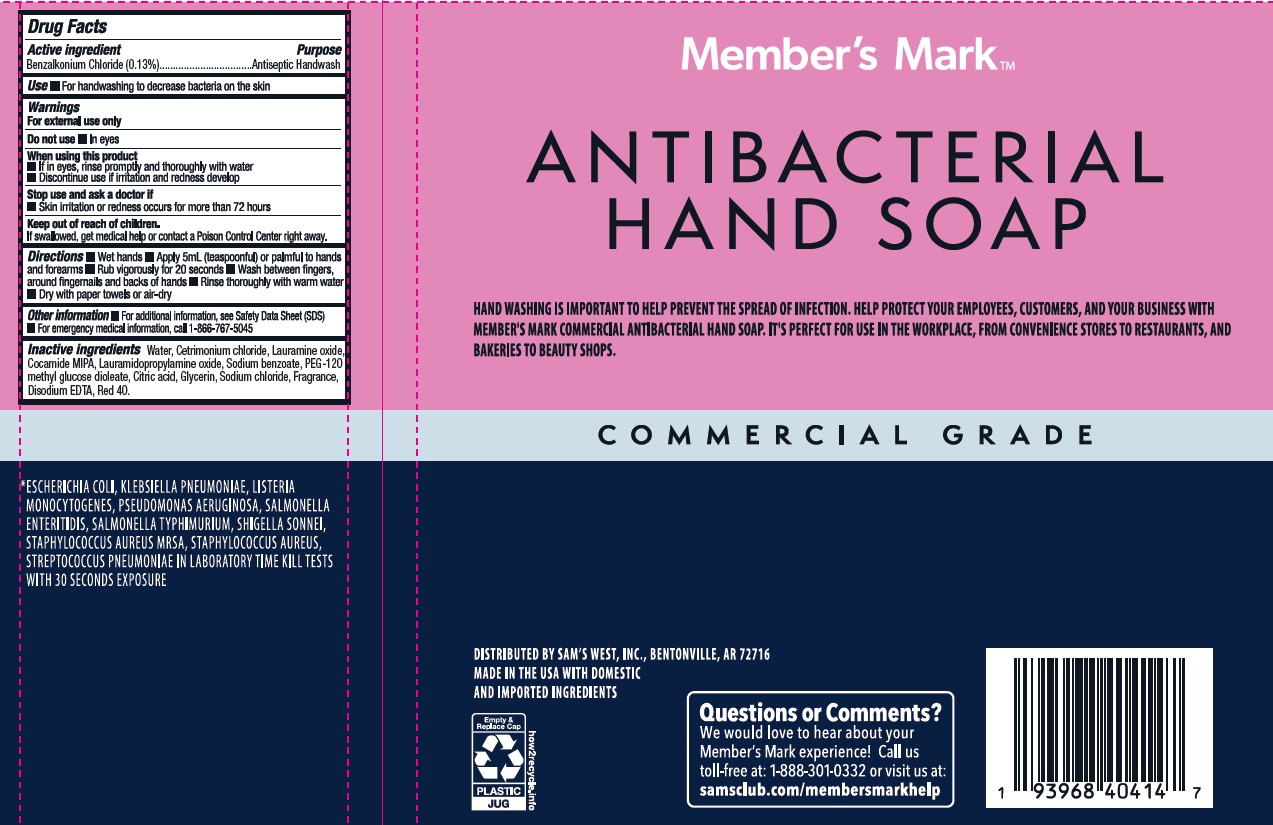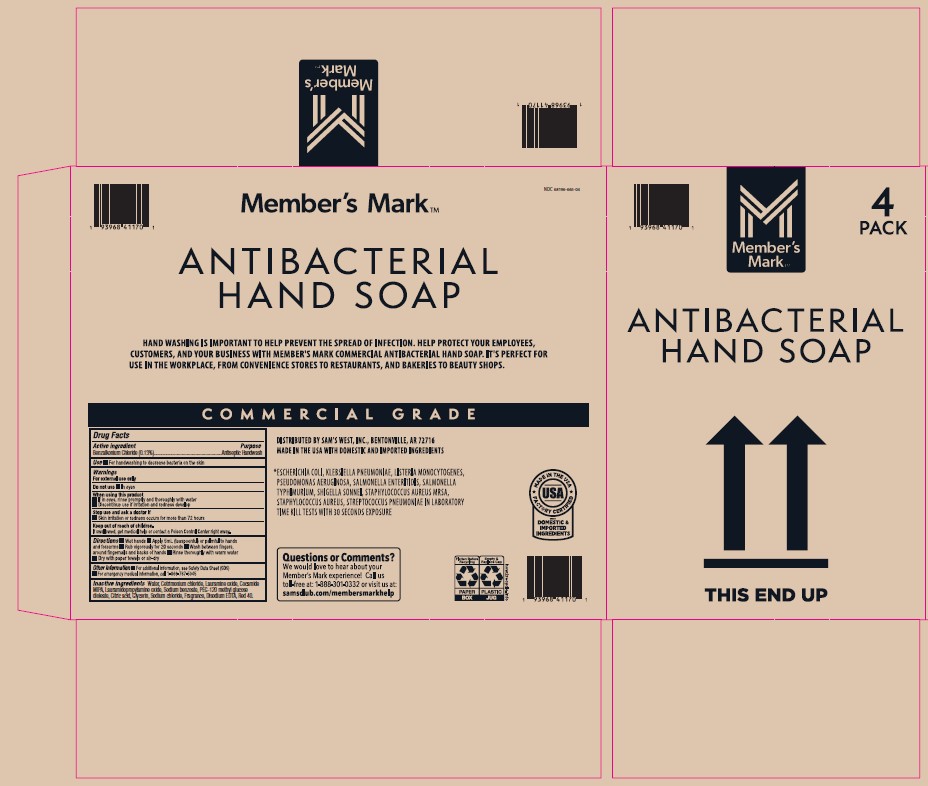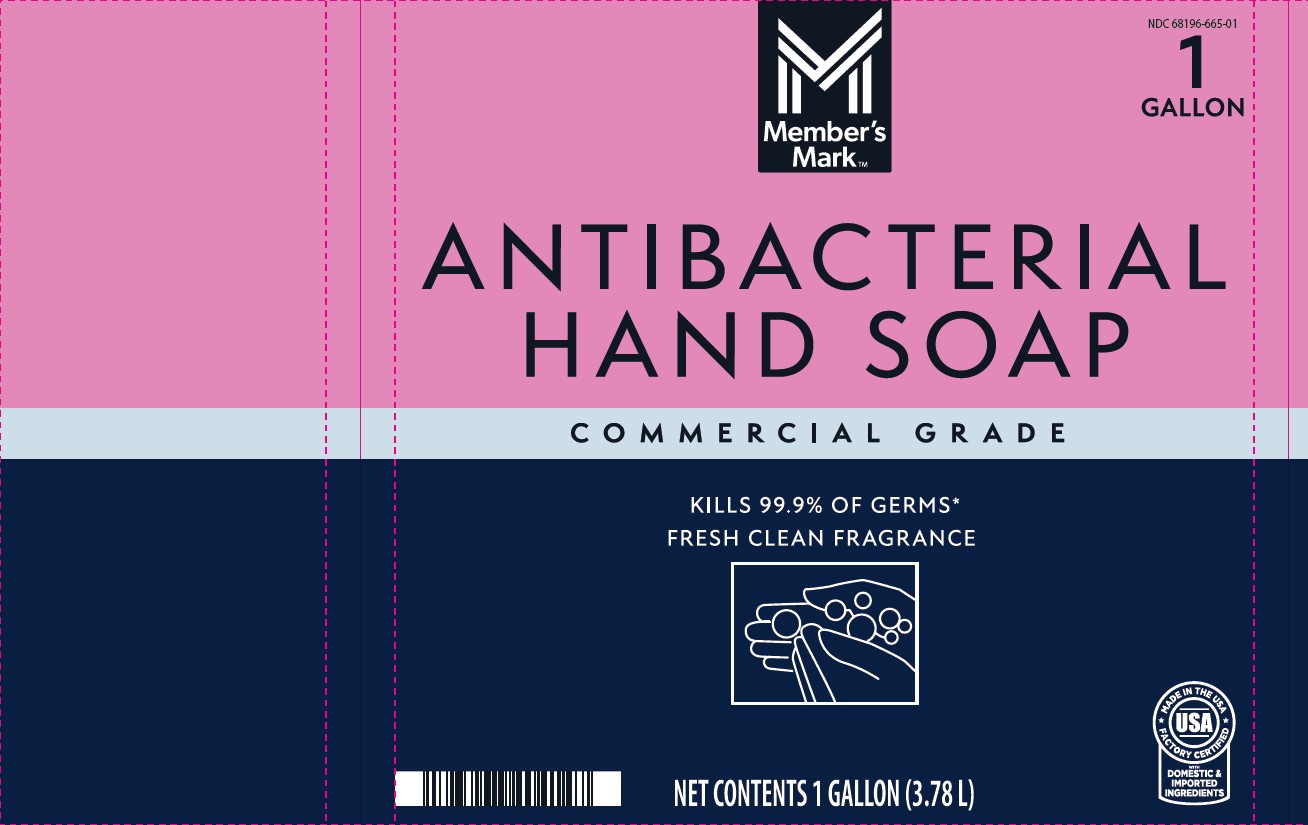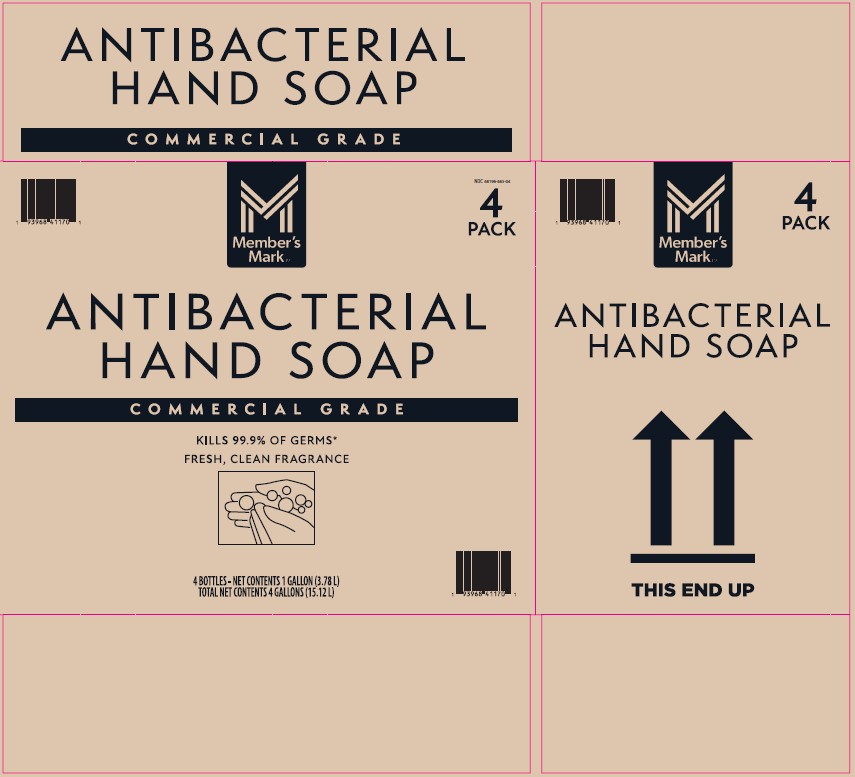 DRUG LABEL: Antibacterial
NDC: 68196-665 | Form: SOLUTION
Manufacturer: Sam's West, Inc.
Category: otc | Type: HUMAN OTC DRUG LABEL
Date: 20241203

ACTIVE INGREDIENTS: BENZALKONIUM CHLORIDE 1.3 g/1000 mL
INACTIVE INGREDIENTS: GLYCERIN; SODIUM BENZOATE; WATER; LAURAMIDOPROPYLAMINE OXIDE; PEG-120 METHYL GLUCOSE DIOLEATE; EDETATE DISODIUM; LAURAMINE OXIDE; CETRIMONIUM CHLORIDE; COCAMIDE MIPA; RED 40; SODIUM CHLORIDE; ANHYDROUS CITRIC ACID

Antibacterial 68196-665

Active ingredient

Benzalkonium Chloride (0.13%)

Purpose

Antiseptic Handwash

Use

- For handwashing to decrease bacteria on skin

Warnings

For external use only

Do not use • In eyes

When using this product

- If in eyes, rinse promptly and thoroughly with water
- Discontinue use if irritation and redness develop

Stop use and ask a doctor if

- Skin irritation or redness occurs for more than 72 hours

Keep out of reach of children.

If swallowed, get medical help or contact a Poison Control Center right away.

Directions

• Wet hands • Apply 5mL (teaspoonful) or palmful to hands and forearms • Rub vigorously for 20 seconds • Wash between fingers, around fingernails and backs of hands • Rinse thoroughly with warm water • Dry with paper towels or air-dry

Other information

• For additional information, see Safety Data Sheet (SDS) • For emergency medical information, call 1-866-767-5045

Inactive ingredients

Water, Cetrimonium chloride, Lauramine oxide, Cocamide MIPA, Lauramidopropylamine oxide, Sodium benzoate, PEG-120 methyl glucose dioleate, Citric acid, Glycerin, Sodium chloride, Fragrance, Disodium EDTA, Red 40.

PACKAGE LABEL

NDC 68196-665-01

1

GALLON

M

Member's

Mark™

ANTIBACTERIAL

HAND SOAP

COMMERCIAL GRADE

KILLS 99.9% OF GERMS*

FRESH CLEAN FRAGRANCE

NET CONTENTS 1 GALLON (3.78 L)